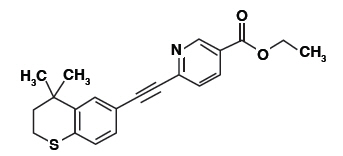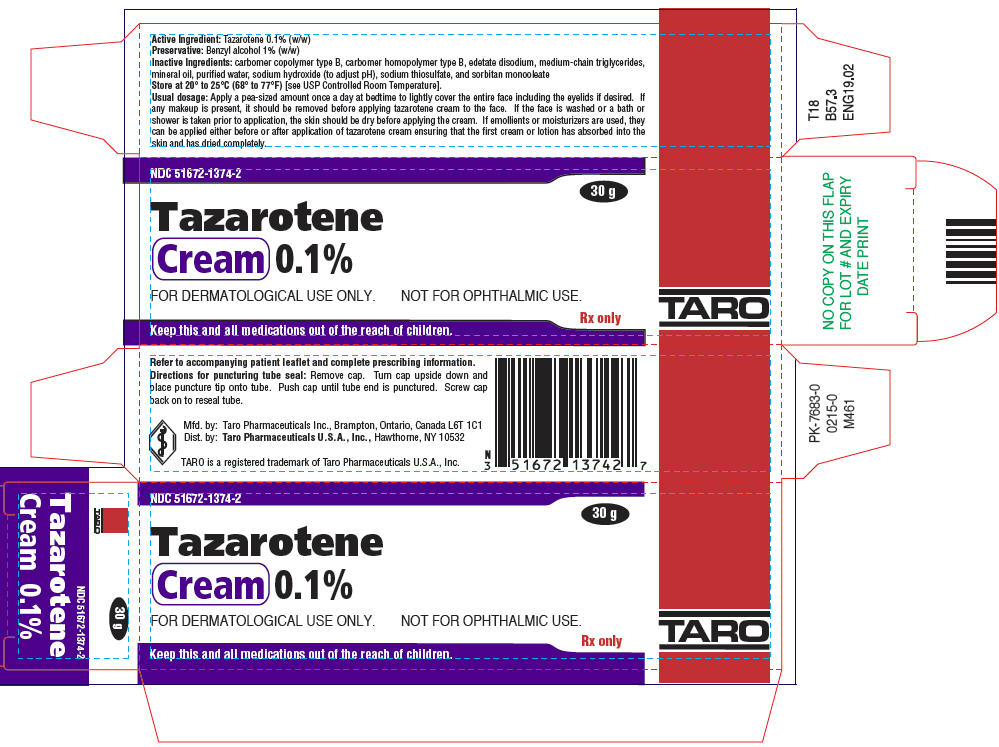 DRUG LABEL: Tazarotene
NDC: 51672-1374 | Form: CREAM
Manufacturer: Sun Pharmaceutical Industries, Inc.
Category: prescription | Type: HUMAN PRESCRIPTION DRUG LABEL
Date: 20250707

ACTIVE INGREDIENTS: TAZAROTENE 1 mg/1 g
INACTIVE INGREDIENTS: BENZYL ALCOHOL; CARBOMER COPOLYMER TYPE B (ALLYL PENTAERYTHRITOL CROSSLINKED); CARBOMER HOMOPOLYMER TYPE B (ALLYL PENTAERYTHRITOL CROSSLINKED); EDETATE DISODIUM; MEDIUM-CHAIN TRIGLYCERIDES; MINERAL OIL; WATER; SODIUM HYDROXIDE; SODIUM THIOSULFATE; SORBITAN MONOOLEATE

HIGHLIGHTS OF PRESCRIBING INFORMATION

These highlights do not include all the information needed to use TAZAROTENE CREAM safely and effectively. See full prescribing information for TAZAROTENE CREAM.
TAZAROTENE cream, for topical use
Initial U.S. Approval: 1997

1 INDICATIONS AND USAGE

Tazarotene cream, 0.1% is a retinoid indicated as an adjunctive agent for use in the mitigation (palliation) of facial fine wrinkling, facial mottled hyper- and hypopigmentation, and benign facial lentigines in patients who use comprehensive skin care and sunlight avoidance programs. (1)

Limitations of Use:

- Does not eliminate or prevent wrinkles or restore more youthful skin. (1)
- Does not repair sun damaged skin or reverse photoaging. (1)
- Safety and effectiveness for the prevention or treatment of actinic keratoses, skin neoplasms, or lentigo maligna have not been established. (1, 5.4)

2 DOSAGE AND ADMINISTRATION

- Apply a pea-sized amount of tazarotene cream to lightly cover the entire face once daily at bedtime. (2)
- If contact with eyes occurs, rinse thoroughly with water. (2)
- Not for ophthalmic, oral, or intravaginal use. (2)

3 DOSAGE FORMS AND STRENGTHS

Cream, 0.1%. (3)

4 CONTRAINDICATIONS

- Pregnancy. (4, 8.1)
- Known Hypersensitivity. (4)

5 WARNINGS AND PRECAUTIONS

- Embryo-Fetal Toxicity:May cause fetal harm when administered to a pregnant woman. Obtain a pregnancy test in females of reproductive potential within 2 weeks prior to initiating treatment. Advise females of reproductive potential to use effective contraception. (5.1)
- Local Irritation:Some individuals may experience excessive pruritus, burning, skin redness, or peeling. If these adverse reactions occur, discontinue tazarotene cream until the integrity of the skin has been restored or reduce dosing interval. Avoid using tazarotene cream on eczematous skin, as such use may cause severe irritation. (5.2)
- Photosensitivity and Risk of Sunburn:Avoid exposure to sunlight, sunlamps, and weather extremes. Wear sunscreen daily. Avoid using tazarotene cream if the patient is also taking drugs known to be photosensitizers. (5.3)
- Lentigo Maligna:Carefully assess facial pigmented lesions of concern before application of tazarotene cream. (5.4)

6 ADVERSE REACTIONS

Most common adverse events (occurring in ≥10% of patients) are desquamation, erythema, burning sensation, dry skin, skin irritation, and pruritus. (6.1)

To report SUSPECTED ADVERSE REACTIONS, contact Taro Pharmaceuticals U.S.A., Inc. at 1-866-923-4914 or FDA at 1-800-FDA-1088 or www.fda.gov/medwatch.

FULL PRESCRIBING INFORMATION

1 INDICATIONS AND USAGE

Tazarotene cream, 0.1% is indicated as an adjunctive agent for use in the mitigation (palliation) of facial fine wrinkling, facial mottled hyper-and hypopigmentation, and benign facial lentigines in patients who use comprehensive skin care and sunlight avoidance programs.

Limitations of Use:

- Tazarotene cream does not eliminate or prevent wrinkles or restore more youthful skin.
- Tazarotene cream does not reverse photoaging or repair sun damaged skin; tazarotene cream does not mitigate coarse or deep wrinkling, tactile roughness, telangiectasia, skin laxity, keratinocytic atypia, melanocytic atypia, or dermal elastosis.
- The safety and the effectiveness of tazarotene cream for the prevention or treatment of actinic keratoses, skin neoplasms, or lentigo maligna have not been established.

2 DOSAGE AND ADMINISTRATION

2.1 Assessment Prior to Treatment Initiation

Obtain a pregnancy test within 2 weeks prior to tazarotene cream therapy. Initiate tazarotene cream therapy during a menstrual period [see Contraindications (4), Warnings and Precautions (5.1), and Use in Specific Populations (8.1, 8.3)] .

Carefully assess facial pigmented lesions of concern by a qualified physician (e.g., dermatologist) before application of tazarotene cream [see Warnings and Precautions (5.4)] .

2.2 Important Administration Instructions

Avoid accidental transfer of tazarotene cream into eyes, mouth, or other mucous membranes. If contact with mucous membranes occurs, rinse thoroughly with water [see Warnings and Precautions (5.2)] .

Wash hands thoroughly after application.

Emollients or moisturizers can be applied either before or after applying tazarotene cream. However, ensure that the first cream or lotion has absorbed into the skin and has dried completely before subsequent cream or lotion application. Use facial moisturizers as frequently as desired [see Warnings and Precautions (5.2)].

Tazarotene cream is for topical use only. Tazarotene cream is not for ophthalmic, oral, or intravaginal use.

Use effective sunscreens and wear protective clothing while using tazarotene cream [see Warnings and Precautions (5.3)].

2.3 Dosage and Administration Instructions

Remove any makeup before applying tazarotene cream to the face. Dry the skin before applying the cream after face washing, bathing, or showering.

Apply a pea-sized amount once a day at bedtime to lightly cover the entire face, including the eyelids, if desired.

Wash hands thoroughly after application.

3 DOSAGE FORMS AND STRENGTHS

Cream: 1 mg of tazarotene per gram (0.1%) of white cream in 30 gram tubes.

4 CONTRAINDICATIONS

Tazarotene cream is contraindicated in:

- Pregnancy. Retinoids may cause fetal harm when administered to a pregnant female [see Warnings and Precautions (5.1), Use in Specific Populations (8.1, 8.3)] .
- Individuals who have known hypersensitivity to any of its components. [see Warnings and Precautions (5.2)].

5 WARNINGS AND PRECAUTIONS

5.1 Embryofetal Toxicity

Based on data from animal reproduction studies, retinoid pharmacology and the potential for systemic absorption, tazarotene cream may cause fetal harm when administered to a pregnant female and is contraindicated during pregnancy .Safety in pregnant females has not been established. The potential risk to the fetus outweighs the potential benefit to the mother from tazarotene cream use during pregnancy; therefore, discontinue tazarotene cream as soon as pregnancy is recognized. Tazarotene elicits malformations and developmental effects associated with retinoids after topical and oral administration to pregnant rats and rabbits during organogenesis. However, limited case reports of pregnancy in females enrolled in clinical trials for tazarotene cream have not reported a clear association with tazarotene and major birth defects or miscarriage risk [see Contraindications (4), Use in Specific Populations (8.1)] .

Systemic exposure to tazarotenic acid is dependent upon the extent of the body surface area treated. In patients treated topically over sufficient body surface area, exposure could be in the same order of magnitude as in these orally treated animals. Although there may be less systemic exposure in the treatment of the face alone due to less surface area for application, tazarotene is a teratogenic substance in animals, and it is not known what level of exposure is required for teratogenicity in humans [see Clinical Pharmacology (12.3)].

Advise pregnant females of the potential risk to a fetus. Obtain a pregnancy test within 2 weeks prior to tazarotene cream therapy. Initiate tazarotene cream therapy during a menstrual period. Advise females of reproductive potential to use effective contraception during treatment with tazarotene cream [see Dosage and Administration (2), Use in Specific Populations (8.3)] .

5.2 Local Irritation and Hypersensitivity Reactions

Local tolerability reactions (including blistering and skin desquamation) and hypersensitivity adverse reactions (including urticaria) have been observed with topical tazarotene. Application of tazarotene cream may cause excessive irritation in the skin of certain sensitive individuals. Some individuals may experience excessive pruritus, burning, skin redness, or peeling. If these adverse reactions occur, discontinue the medication until the integrity of the skin is restored, or reduce the dosing to an interval the patient can tolerate. Closely monitor the frequency of application by carefully observing the therapeutic response and skin tolerance.

Avoid concomitant use of topical medications and cosmetics that have a strong drying effect. It is also advisable to "rest" a patient's skin until the effects of such preparations subside before use of tazarotene cream is begun.

Avoid using tazarotene cream on eczematous skin because such use may cause severe irritation.

Weather extremes, such as wind or cold, may be more irritating to patients using tazarotene cream.

5.3 Photosensitivity and Risk of Sunburn

Because of heightened burning susceptibility, minimize exposure to ultraviolet rays (including sunlight and sun lamps) during the use of tazarotene cream. Patients must be warned to use sunscreens and protective clothing when using tazarotene cream. Advise patients with sunburn not to use tazarotene cream until the sunburn is fully recovered.

Patients who may have considerable sun exposure because of their occupation and those patients with inherent sensitivity to sunlight should exercise particular caution when using tazarotene cream.

Avoid using tazarotene cream if the patient is also taking drugs known to be photosensitizers (e.g., thiazides, tetracyclines, fluoroquinolones, phenothiazines, sulfonamides) because of the increased possibility of augmented photosensitivity.

5.4 Lentigo Maligna

Some facial pigmented lesions are not lentigines, but rather lentigo maligna, a type of melanoma. Before application of tazarotene cream, carefully assess facial pigmented lesions of concern by a qualified physician (e.g., dermatologist) to exclude a diagnosis of lentigo maligna.

6 ADVERSE REACTIONS

The following serious adverse reactions are discussed in more detail in other sections of the labeling:

- Embryofetal toxicity [see Warnings and Precautions (5.1)]
- Photosensitivity and Risk of Sunburn [see Warnings and Precautions (5.3)]

6.1 Clinical Trials Experience

Because clinical trials are conducted under widely varying conditions, adverse reaction rates observed in the clinical trials of a drug cannot be directly compared to rates in the clinical trials of another drug and may not reflect the rates observed in clinical practice.

The most frequent adverse reactions reported with tazarotene cream, 0.1% that occurred in greater than 10% of subjects, included desquamation, erythema, burning sensation, and dry skin (in descending order). Reactions that occurred in 1 to 10% of subjects, included skin irritation, pruritus, irritant contact dermatitis, stinging, rash, and cheilitis (in descending order). Common adverse events that occurred at a rate of at least 1% and at a higher rate in the tazarotene cream group than in the vehicle group in the clinical trials are presented in the following table.

TABLE OF ADVERSE EVENTS SEEN IN 24-WEEK CLINICAL TRIALS WITH TAZAROTENE CREAM 0.1%
Adverse Event | Tazarotene Cream, 0.1% N=567 | Vehicle N=564
Desquamation | 40% | 3%
Erythema | 34% | 3%
Burning Sensation | 26% | <1%
Dry Skin | 16% | 3%
Irritation Skin | 10% | 1%
Pruritus | 10% | 1%
Irritant Contact Dermatitis | 8% | 1%
Stinging | 3% | <1%
Rash | 3% | 1%
Cheilitis | 1% | 0%

A few subjects reported adverse events at Week 0; however, for patients who were treated with tazarotene cream, the highest number of new reports for each adverse event was at Week 2.

When combining data from the two trials, 5.3% of subjects in the tazarotene cream group and 0.9% of subjects in the vehicle group discontinued because of adverse events.

Overall, 20/567 (3.5%) subjects in the tazarotene cream group and 16/564 (2.8%) subjects in the vehicle group reported adverse events (including edema, irritation, and inflammation) directly related to the eye or eyelid.

The majority of these conditions were mild.

6.2 Postmarketing Experience

The following adverse reactions have been identified during postapproval use of tazarotene. Because these reactions are reported voluntarily from a population of uncertain size, it is not always possible to reliably estimate their frequency or establish a causal relationship to drug exposure.

Skin and subcutaneous tissue disorders:blister, dermatitis, urticaria, skin exfoliation, skin discoloration (including skin hyperpigmentation or skin hypopigmentation), swelling at or near application sites, and pain.

7 DRUG INTERACTIONS

No formal drug-drug interaction studies were conducted with tazarotene cream.

In a trial of 27 healthy female subjects between the ages of 20 to 55 years receiving a combination oral contraceptive tablet containing 1 mg norethindrone and 35 mcg ethinyl estradiol, concomitant use of tazarotene administered as 1.1 mg orally (mean ± SD Cmaxand AUC0-24of tazarotenic acid were 28.9 ± 9.4 ng/mL and 120.6 ± 28.5 ng*h/mL) did not affect the pharmacokinetics of norethindrone and ethinyl estradiol over a complete cycle.

The impact of tazarotene on the pharmacokinetics of progestin only oral contraceptives (i.e., minipills) has not been evaluated.

8 USE IN SPECIFIC POPULATIONS

8.1 Pregnancy

Risk Summary

Based on data from animal reproduction studies, retinoid pharmacology, and the potential for systemic absorption, tazarotene cream may cause fetal harm when administered to a pregnant female and is contraindicated during pregnancy. Safety in pregnant females has not been established. The potential risk to the fetus outweighs the potential benefit to the mother from tazarotene cream during pregnancy; therefore, tazarotene cream should be discontinued as soon as pregnancy is recognized [see Contraindications (4), Warnings and Precautions (5.1), Clinical Pharmacology (12.3)]. Limited case reports of pregnancy in females enrolled in clinical trials for tazarotene cream have not established a clear association with tazarotene and major birth defects or miscarriage risk. Because the exact timing and extent of exposure in relation to the gestational age are not certain, the significance of these findings is unknown .

In animal reproduction studies with pregnant rats, tazarotene dosed topically during organogenesis at 2 times the maximum systemic exposure in subjects treated with the maximum recommended human dose (MRHD) of tazarotene cream, 0.1% resulted in reduced fetal body weights and reduced skeletal ossification. In animal reproduction studies with pregnant rabbits dosed topically with tazarotene gel at 26 times the maximum systemic exposure in subjects treated with the MRHD of tazarotene cream, 0.1%, there was a single incident of known retinoid malformations, including spina bifida, hydrocephaly, and heart anomalies.

In animal reproduction studies with pregnant rats and rabbits, tazarotene dosed orally during organogenesis at 2 and 52 times, respectively, the maximum systemic exposure in subjects treated with the MRHD of tazarotene cream, 0.1% resulted in malformations, fetal toxicity, developmental delays, and/or behavioral delays .In pregnant rats, tazarotene dosed orally prior to mating through early gestation resulted in decreased litter size, decreased numbers of live fetuses, decreased fetal body weights, and increased malformations at doses approximately 7 times higher than the maximum systemic exposure in subjects treated with the MRHD of tazarotene cream, 0.1% [see Data].

The background risk of major birth defects and miscarriage for the indicated population is unknown. Adverse outcomes in pregnancy occur regardless of the health of the mother or the use of medications. In the U.S. general population, the estimated background risk of major birth defects and miscarriage in clinically recognized pregnancies is 2 to 4% and 15 to 20%, respectively.

Data

Animal Data

In rats, a tazarotene 0.05% gel formulation dosed topically during gestation days 6 through 17 at 0.25 mg/kg/day, which represented 2 times the maximum systemic exposure in subjects treated with the MRHD of tazarotene cream, 0.1% (i.e., 2 mg/cm^2over a 15% body surface area), resulted in reduced fetal body weights and reduced skeletal ossification. Rabbits dosed topically with 0.25 mg/kg/day tazarotene gel, which represented 26 times the maximum systemic exposure in subjects treated with the MRHD of tazarotene cream, 0.1%, during gestation days 6 through 18, had a single incident of known retinoid malformations, including spina bifida, hydrocephaly, and heart anomalies.

When tazarotene was given orally to animals, developmental delays were seen in rats, and malformations and post-implantation loss were observed in rats and rabbits at doses representing 2 and 52 times, respectively, the maximum systemic exposure seen in subjects treated with the MRHD of tazarotene cream, 0.1%.

In female rats orally administered 2 mg/kg/day of tazarotene from 15 days before mating through gestation day 7, which represented 7 times the maximum systemic exposure in subjects treated with the MRHD of tazarotene cream, 0.1%, classic developmental effects of retinoids were observed including decreased number of implantation sites, decreased litter size, decreased numbers of live fetuses, and decreased fetal body weights. A low incidence of retinoid-related malformations was observed at that dose.

In a pre- and postnatal development toxicity study, topical administration of tazarotene gel (0.125 mg/kg/day) to pregnant female rats from gestation day 16 through lactation day 20 reduced pup survival, but did not affect the reproductive capacity of the offspring. Based on data from another study, the maximum systemic exposure in the rat would be equivalent to the maximum systemic exposure in subjects treated with the MRHD of tazarotene cream, 0.1%.

8.2 Lactation

Risk Summary

There is no information regarding the presence of tazarotene in human milk, the effects on the breastfed infant, or the effects on milk production. After single topical doses of 14C-tazarotene gel to the skin of lactating rats, radioactivity was detected in rat milk. The lack of clinical data during lactation precludes a clear determination of the risk of tazarotene cream to an infant during lactation; therefore, the developmental and health benefits of breastfeeding should be considered along with the mother's clinical need for tazarotene cream and any potential adverse effects on the breastfed child from tazarotene cream or from the underlying maternal condition.

8.3 Females and Males of Reproductive Potential

Pregnancy Testing

Pregnancy testing is recommended for females of reproductive potential within 2 weeks prior to initiating tazarotene cream therapy which should begin during a menstrual period.

Contraception

Females

Based on animal studies, tazarotene cream may cause fetal harm when administered to a pregnant woman [see Use in Specific Populations (8.1)]. Advise females of reproductive potential to use effective contraception during treatment with tazarotene cream.

8.4 Pediatric Use

The safety and efficacy of tazarotene cream have not been established in patients under the age of 17 years with facial fine wrinkling, facial mottled hyper- and hypopigmentation, and benign facial lentigines.

8.5 Geriatric Use

In the studies of facial fine wrinkling, facial mottled hyper- and hypopigmentation, and benign facial lentigines, 44 male subjects and 180 female subjects out of the total population of 1131 subjects were older than 65 years of age. No overall differences in safety or effectiveness were observed between these subjects and younger subjects, and other clinical experience has not identified differences in responses between the elderly and younger subjects, but greater sensitivity of some older individuals cannot be ruled out.

10 OVERDOSAGE

Tazarotene cream is not for oral use. Oral ingestion of the drug may lead to the same adverse effects as those associated with excessive oral intake of Vitamin A (hypervitaminosis A) or other retinoids. If oral ingestion occurs, monitor the patient closely and administer appropriate supportive measures, as necessary.

11 DESCRIPTION

Tazarotene cream, 0.1% is for topical use and contains the active ingredient, tazarotene. Each gram of tazarotene cream, 0.1% contains 1 mg of tazarotene in a white cream base.

Tazarotene is a member of the acetylenic class of retinoids. Chemically, tazarotene is ethyl 6-[2-(4,4-dimethylthiochroman-6-yl)ethynyl] nicotinate. The compound has an empirical formula of C21H21NO2S and molecular weight of 351.46. The structural formula is shown below:

Tazarotene Cream contains the following inactive ingredients: carbomer copolymer type B, carbomer homopolymer type B, edetate disodium, medium-chain triglycerides, mineral oil, purified water, sodium hydroxide (to adjust pH), sodium thiosulfate, and sorbitan monooleate.

12 CLINICAL PHARMACOLOGY

12.1 Mechanism of Action

Tazarotene is a retinoid prodrug which is converted to its active form, the carboxylic acid of tazarotene, by deesterification. Tazarotenic acid binds to all three members of the retinoic acid receptor (RAR) family: RARα, RARβ, and RARγ, but shows relative selectivity for RARβ and RARγ, and may modify gene expression. The clinical significance of these findings for the mitigation of facial fine wrinkling, facial mottled hyper- and hypopigmentation, and benign facial lentigines is unknown.

12.3 Pharmacokinetics

Following topical application, tazarotene undergoes esterase hydrolysis to form its active metabolite, tazarotenic acid. Little parent compound could be detected in the plasma. Tazarotenic acid was highly bound to plasma proteins (greater than 99%). Tazarotene and tazarotenic acid were metabolized to sulfoxides, sulfones, and other polar metabolites which were eliminated through urinary and fecal pathways. The half-life of tazarotenic acid was approximately 18 hours.

Tazarotene cream 0.1% was topically applied once daily over four weeks to either the face (6 females and 2 males) or to 15% of body surface area (8 females and 8 males) in subjects with fine wrinkling and mottled hyperpigmentation. In the "face-only" dosing group, the maximum average Cmaxand AUC0-24hrvalues of tazarotenic acid occurred on Day 15 with mean ± SD values of Cmaxand AUC0-24hrof tazarotenic acid being 0.236 ± 0.255 ng/mL (N=8) and 2.44 ± 1.38 ng∙hr/mL (N=8), respectively. The mean Cmaxand AUC0-24hrvalues of tazarotenic acid from subjects in the 15% body surface area dosing group were approximately 10 times higher than those from subjects in the face-only dosing group. The single highest Cmaxthroughout the trial period was 3.43 ng/mL on day 29 from subjects in the 15% body surface area dosing group. Gender had no influence on the systemic bioavailability of tazarotenic acid.

Blood samples were collected from one of the two phase 3 trials to evaluate the systemic exposure following application of tazarotene cream 0.1% once daily for 24 weeks (double-blind period) followed by 28 weeks (open-label) under clinical conditions. The mean plasma tazarotenic acid concentrations, following topical treatment with tazarotene cream 0.1% over 52 weeks, ranged between 0.092 ± 0.073 ng/mL and 0.127 ± 0.142 ng/mL. The single highest observed tazarotenic acid concentration throughout the 52-week trial was 0.705 ng/mL (observed at week 36). Systemic availability of tazarotenic acid was minimal and remained steady following once daily application of tazarotene cream 0.1% to the faces of subjects in the trial for up to 52 weeks.

13 NONCLINICAL TOXICOLOGY

13.1 Carcinogenesis, Mutagenesis, Impairment of Fertility

A long term study of tazarotene following oral administration of 0.025 mg/kg/day, 0.050 mg/kg/day, and 0.125 mg/kg/day to rats showed no indications of increased carcinogenic risks. Based on pharmacokinetic data from a shorter term study in rats, the highest dose of 0.125 mg/kg/day was anticipated to give systemic exposure in the rat equivalent to the maximum systemic exposure in subjects treated with the MRHD of tazarotene cream 0.1%.

A long-term topical application study of up to 0.1% tazarotene in a gel formulation in mice, terminated at 88 weeks, showed that dose levels of 0.05 mg/kg/day, 0.125 mg/kg/day, 0.25 mg/kg/day, and 1 mg/kg/day (reduced to 0.5 mg/kg/day for males after 41 weeks due to severe dermal irritation) revealed no apparent carcinogenic effects when compared to vehicle control animals. Systemic exposure at the highest dose represented 8 times the maximum systemic exposure in subjects treated with the MRHD of tazarotene cream 0.1%.

Tazarotene was non-mutagenic in the Ames assay and did not produce structural chromosomal aberrations in a human lymphocyte assay. Tazarotene was also non-mutagenic in the CHO/HGPRT mammalian cell forward gene mutation assay and was non-clastogenic in the in vivomouse micronucleus test.

No impairment of fertility occurred in rats when male animals were treated for 70 days prior to mating and female animals were treated for 14 days prior to mating and continuing through gestation and lactation with topical doses of tazarotene gel up to 0.125 mg/kg/day. Based on data from another study, the systemic drug exposure in the rat would be equivalent to the maximum systemic exposure in subjects treated with the MRHD of tazarotene cream 0.1%.

No impairment of mating performance or fertility was observed in male rats treated for 70 days prior to mating with oral doses of up to 1 mg/kg/day tazarotene, which represented 4 times the maximum systemic exposure in subjects treated with the MRHD of tazarotene cream 0.1%.

No effect on parameters of mating performance or fertility was observed in female rats treated for 15 days prior to mating and continuing through day 7 of gestation with oral doses of tazarotene up to 2 mg/kg/day. However, there was a significant decrease in the number of estrous stages and an increase in developmental effects at that dose, which represented 7 times the maximum systemic exposure in subjects treated with the MRHD of tazarotene cream 0.1% [see Use in Specific Populations (8.1)] .

14 CLINICAL STUDIES

Two double-blind, randomized vehicle-controlled trials (Trial 1 and Trial 2) enrolled 1131 subjects with mild to severe fine wrinkling, facial mottled hyper- and hypo-pigmentation, and benign facial lentigines because of sun overexposure. Both trials compared the application of tazarotene cream 0.1% to its vehicle once daily for 24 weeks to the facial skin. Treatment was as an adjunct to a comprehensive skin care and sun avoidance program that included use of sunscreens, protective clothing, and non-prescription emollient cream.

In both trials, the endpoint was the proportion of subjects achieving an improvement of at least one grade from baseline in fine wrinkling, mottled hypo- and hyper-pigmentation, and benign facial lentigines. At two to four week intervals, the severity of fine wrinkling, mottled hyper-and hypo-pigmentation, and benign facial lentigines were graded on a using a 5-point photonumeric scale (0 = none, 1 = minimal, 2 = mild, 3 = moderate, and 4 = severe).

Of 1131 subjects, approximately 97% of subjects in clinical trials were white (Caucasian) with 80% of subjects in the clinical studies having Fitzpatrick skin type classifications I-III. The distribution of subject skin types were: Type I –12%; Type II – 26%; Type III – 40%; and Type IV 22%. Subjects with skin types V and VI were not studied. Insufficient number of non-white subjects (Asian, Hispanic, or other) were studied to make an adequate determination of efficacy of tazarotene cream in such subjects.

Percentage of Subjects with Improvement in Fine Wrinkling after 24 Weeks of Treatment
 | Trial 1 |  | Trial 2
 | Tazarotene Cream, 0.1% N=283 | Vehicle N=280 | Tazarotene Cream, 0.1% N=284 | Vehicle N=284
2 or more Grades Improvement | 5% | 1% | 13% | 5%
1 Grade Improvement | 35% | 15% | 45% | 18%
No Change | 59% | 83% | 42% | 76%
Worsened | 1% | 1% | 0% | 1%

Fine Wrinkling was graded on a 5-point scale (0=none, 1=minimal, 2=mild, 3=moderate, 4=severe) using a photonumeric guideline for investigators.

Percentage of Subjects with Improvement in Mottled Hyperpigmentation after 24 Weeks of Treatment
 | Trial 1 |  | Trial 2
 | Tazarotene Cream, 0.1% N=283 | Vehicle N=280 | Tazarotene Cream, 0.1% N=284 | Vehicle N=284
2 or more Grades Improvement | 17% | 1% | 28% | 10%
1 Grade Improvement | 42% | 17% | 54% | 30%
No Change | 41% | 80% | 18% | 59%
Worsened | <1% | 3% | <1% | 1%

Mottled hyperpigmentation was graded on a 5-point scale (0=none, 1=minimal, 2=mild, 3=moderate, 4=severe) using a photonumeric guideline for investigators.

In the 24 week trials, efficacy was also demonstrated in mottled hypopigmentation and benign facial lentigines, which were secondary endpoints in those trials.

The duration of the mitigating effects on facial fine wrinkling, mottled hyper- and hypopigmentation, and benign facial lentigines following discontinuation of tazarotene cream has not been studied.

16 HOW SUPPLIED/STORAGE AND HANDLING

Tazarotene cream 0.1%, containing 1 mg of tazarotene per gram of white cream is available in a 30 gram collapsible aluminum tube with a tamper-evident aluminum membrane over the opening and a white polypropylene screw cap. NDC 51672-1374-2

STORAGE AND HANDLING

Storage: Store at 20° to 25°C (68° to 77°F)[See USP Controlled Room Temperature].

17 PATIENT COUNSELING INFORMATION

Advise the patient to read the FDA-approved patient labeling (Patient Information).

Embryofetal Toxicity

Inform females of reproductive potential of the potential risk to a fetus. Advise these patients to use effective contraception during treatment with tazarotene cream. Advise patients to inform their healthcare provider of a known or suspected pregnancy [see Warnings and Precautions (5.1)and Use in Specific Populations (8.1, 8.3)].

Photosensitivity and Risk of Sunburn

Advise patients to avoid excessive sun exposure and to use of sunscreens and protective measures (hat, visor). Advise patients to avoid using tazarotene if also taking other medicines may increase sensitivity to sunlight.

Important Administration Instructions

Advise patients of the following:

1. Use tazarotene cream on the face once per day, at bedtime.
2. Tazarotene cream is for topical use only. Do not apply to eyes, mouth, or other mucous membranes. The cream may cause severe redness, itching, burning, stinging, and peeling. Avoid accidental transfer of tazarotene cream into eyes, mouth, or other mucous membranes. If contact with mucous membranes occurs, rinse thoroughly with water. Seek medical attention if eye irritation continues. Wash hands thoroughly after applying tazarotene cream.
3. Gently wash face with a mild soap before applying the cream.
4. Dry skin before applying the cream.
5. Apply only a small pea sized amount (about ¼ inch or 5 millimeter diameter) to lightly cover the entire face.
6. Apply emollients or moisturizers before or after tazarotene cream and ensure that the first cream or lotion has absorbed into the skin and dried completely.
7. In the morning, apply a moisturizing sunscreen.

Manufactured by: Taro Pharmaceuticals Inc., Brampton, Ontario, Canada L6T 1C1

Distributed by: Taro Pharmaceuticals U.S.A., Inc.,Hawthorne, NY 10532

Revised: August 2017
PK-7689-3
0817-3
10

PATIENT INFORMATION
Tazarotene (taz-AR-oh-teen) Cream, 0.1%

Important information:Tazarotene cream is for use on skin only. Do not use tazarotene cream in your eyes, mouth, or vagina.

What is the most important information I should know about tazarotene cream?

Tazarotene cream may cause birth defects if used during pregnancy.

- Females must not be pregnant when they start using tazarotene cream or become pregnant during treatment with tazarotene cream.
- For females who are able to get pregnant:
  - Your doctor will order a pregnancy test for you within 2 weeks before you begin treatment with tazarotene cream to be sure that you are not pregnant. Your doctor will decide when to do the test.
  - Begin treatment with tazarotene cream during a normal menstrual period.
  - Use an effective form of birth control during treatment with tazarotene cream. Talk with your doctor about birth control options that may be used to prevent pregnancy during treatment with tazarotene cream.
  - Stop using tazarotene cream and tell your doctor right away if you become pregnant while using tazarotene cream.

What is tazarotene cream?

Tazarotene cream is a prescription medicine used on the skin (topical) that may reduce fine facial wrinkles and certain types of dark and light spots on the face in people who use a total skin care program and avoid sunlight.

- Tazarotene cream does not remove or prevent wrinkles, repair sun damaged skin, reverse skin aging from the sun (photoaging), or bring back more youthful or younger skin.
- Tazarotene cream does not work for everyone who uses it. It may work better for some people than for others.
- It is not known if tazarotene cream is safe and effective for the prevention or treatment of certain other skin problems.
- It is not known if tazarotene cream is safe and effective in children under 17 years of age with facial fine wrinkles and certain types of dark and light spots on the face.

Who should not use tazarotene cream?

Do not use tazarotene cream if you:

- are pregnant or plan to become pregnant. See " What is the most important information I should know about tazarotene cream?" at the beginning of this leaflet.
- are allergic to any of the ingredients in tazarotene cream. See the end of this leaflet for a complete list of ingredients in tazarotene cream.

What should I tell my doctor before using tazarotene cream?

Before you use tazarotene cream, tell your doctor about all of your medical conditions, including if you:

- have eczema or any other skin problems, including skin cancers
- are breastfeeding or plan to breastfeed. It is not known if tazarotene cream passes into your breast milk. Talk to your doctor about using tazarotene cream while breastfeeding.

Tell your doctor about all the medicines you take, including prescription and over-the-counter medicines, vitamins, and herbal supplements.

Certain medicines, vitamins, or supplements may make your skin more sensitive to sunlight.
Also, tell your doctor about any cosmetics you use, including moisturizers, creams, lotions, or products that can dry out your skin.

How should I use tazarotene cream?

- Use tazarotene cream exactly as your doctor tells you to use it.
- Apply tazarotene cream 1 time a day, at bedtime.
- Do not get tazarotene cream in your eyes. If tazarotene cream gets in your eyes, rinse them well with water. Call your doctor or get medical help if you have eye irritation that does not go away.
- Wash your hands after applying tazarotene cream.

Follow these instructions for applying tazarotene cream:

- Gently wash your face with mild soap. Be sure to remove any makeup. Rinse and pat your skin dry.
- Apply a pea-sized amount to lightly cover your face. You can include your eyelids, if desired.
- In the morning, apply a moisturizing sunscreen.
- You can use a cream or lotion to soften or moisten your skin before or after you apply tazarotene cream. Make sure that the first cream or lotion has absorbed into your skin and dried completely before you apply the second product.
- You can use facial moisturizers, such as lotions, oils, and creams, as often as you want.
- If you swallow tazarotene cream, call your doctor or go to the nearest emergency room right away.

What should I avoid while using tazarotene cream?

- Avoid sunlight, including sunlamps, during treatment with tazarotene cream. Tazarotene cream can make you more sensitive to the sun, and the light from sunlamps and tanning beds. You could get a severe sunburn. Use sunscreen and wear a hat and clothes that cover your skin if you have to be in sunlight.
- Talk to your doctor if you get a sunburn during treatment with tazarotene cream. If you get a sunburn, do not use tazarotene cream until your sunburn is healed.
- Avoid using cosmetics or topical medicines that may make your skin more sensitive to sunlight or make your skin dry.
- Avoid using tazarotene cream on skin with eczema because it may cause severe irritation.

What are the possible side effects of tazarotene cream?

Tazarotene cream may cause serious side effects, including:

- Skin irritation and allergic reactions (hypersensitivity).Tazarotene cream may cause increased skin irritation and hives. Tell your doctor if you develop hives, or itching, burning, redness, or peeling of your skin during treatment with tazarotene cream. If you develop hives or skin irritation, your doctor may tell you to stop using tazarotene cream until your skin heals or tell you to use tazarotene cream less often. Also, wind or cold weather may be more irritating to your skin while you are using tazarotene cream
- Sensitivity to sunlight and risk of sunburn.See " What should I avoid while using tazarotene cream?"

The most common side effects of tazarotene cream includepeeling, redness, burning, dry or irritated skin, and itching.
These are not all the side effects possible with tazarotene cream.
Call your doctor for medical advice about side effects. You may report side effects to FDA at 1-800-FDA-1088.

How should I store tazarotene cream?

- Store tazarotene cream at 77°F (25°C).
- Keep tazarotene cream and all medicines out of reach of children.

General information about the safe and effective use of tazarotene cream.

Medicines are sometimes prescribed for purposes other than those listed in a Patient Information leaflet. Do not use tazarotene cream for a condition for which it was not prescribed. Do not give tazarotene cream to other people, even if they have the same symptoms that you have. It may harm them. You can ask your pharmacist or doctor for information about tazarotene cream that is written for health professionals.

What are the ingredients of tazarotene cream?

Active ingredient:tazarotene

Inactive ingredients:carbomer copolymer type B, carbomer homopolymer type B, edetate disodium, medium-chain triglycerides, mineral oil, purified water, sodium hydroxide (to adjust pH), sodium thiosulfate, and sorbitan monooleate.

Manufactured by: Taro Pharmaceuticals Inc., Brampton, Ontario, Canada L6T 1C1

Distributed by: Taro Pharmaceuticals U.S.A., Inc.,Hawthorne, NY 10532

Revised: August 2017 PK-7689-3 0817-3 10

This Patient Information has been approved by the U.S. Food and Drug Administration

PRINCIPAL DISPLAY PANEL - 30 g Tube Carton

NDC 51672-1374-2

30 g

Tazarotene
Cream 0.1%

FOR DERMATOLOGICAL USE ONLY.
NOT FOR OPHTHALMIC USE.

Rx only

Keep this and all medications out of the reach of children.

TARO